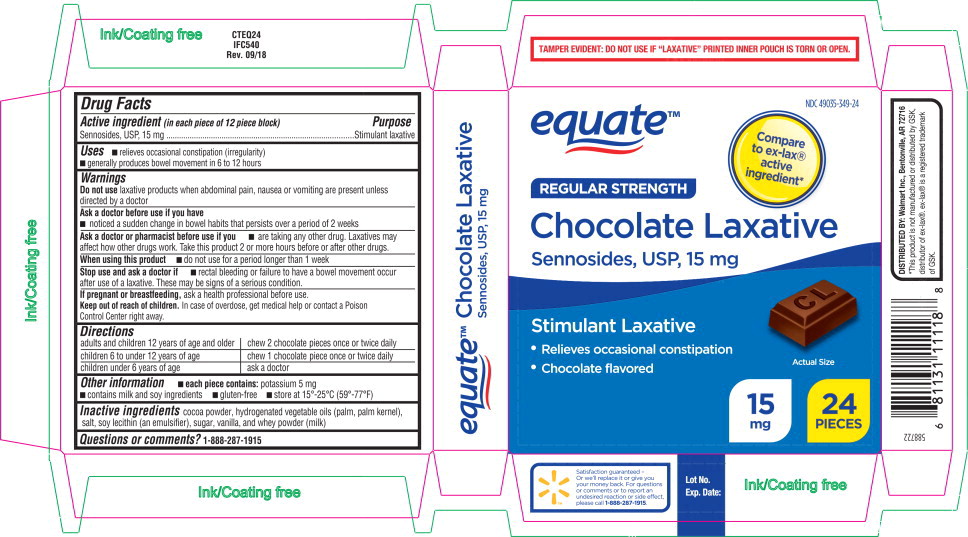 DRUG LABEL: Chocolate Laxative 
NDC: 49035-349 | Form: TABLET, CHEWABLE
Manufacturer: Wal-Mart Stores Inc
Category: otc | Type: HUMAN OTC DRUG LABEL
Date: 20241223

ACTIVE INGREDIENTS: Sennosides 15 mg/1 1
INACTIVE INGREDIENTS: cocoa; cotton seed; palm kernel oil; sodium chloride; lecithin, soybean; sucrose; vanilla; whey

Drug Facts

Active ingredient (in each piece of 12 piece block)

Sennosides, USP, 15 mg

Purpose

Stimulant laxative

Uses

- relieves occasional constipation (irregularity)
- generally produces bowel movement in 6 to 12 hours

Warnings

Do not use laxative products when abdominal pain, nausea or vomiting are present unless directed by a doctor

Ask a doctor before use if you have

- noticed a sudden change in bowel habits that persists over a period of 2 weeks

Ask a doctor or pharmacist before use if you

- are taking any other drug. Laxatives may affect how other drugs work. Take this product 2 or more hours before or after other drugs.

When using this product

- do not use for a period longer than 1 week

Stop use and ask a doctor if

- rectal bleeding or failure to have a bowel movement occur after use of a laxative. These may be signs of a serious condition.

PREGNANCY OR BREAST FEEDING

If pregnant or breastfeeding, ask a health professional before use.

Keep out of reach of children. In case of overdose, get medical help or contact a Poison Control Center right away.

Directions

adults and children 12 years of age and older | chew 2 chocolate pieces once or twice daily
children 6 to under 12 years of age | chew 1 chocolate piece once or twice daily
children under 6 years of age | ask a doctor

Other information

- each piece contains: potassium 5 mg
- contains milk and soy ingredients
- gluten-free
- store at 15°-25°C (59°-77°F)

Inactive ingredients

cocoa powder, hydrogenated vegetable oils (palm, palm kernel), salt, soy lecithin (an emulsifier), sugar, vanilla, and whey powder (milk)

Questions or comments?

1-888-287-1915

Principal Display Panel - 15 mg Carton Label

equate™

NDC 49035-349-24

Compare
to ex-lax®
active
ingredient*

REGULAR STRENGTH
Chocolate Laxative

Sennosides, USP, 15 mg

Stimulant Laxative

- Relieves occasional constipation
- Chocolate flavored

Actual Size

15
mg

24
PIECES